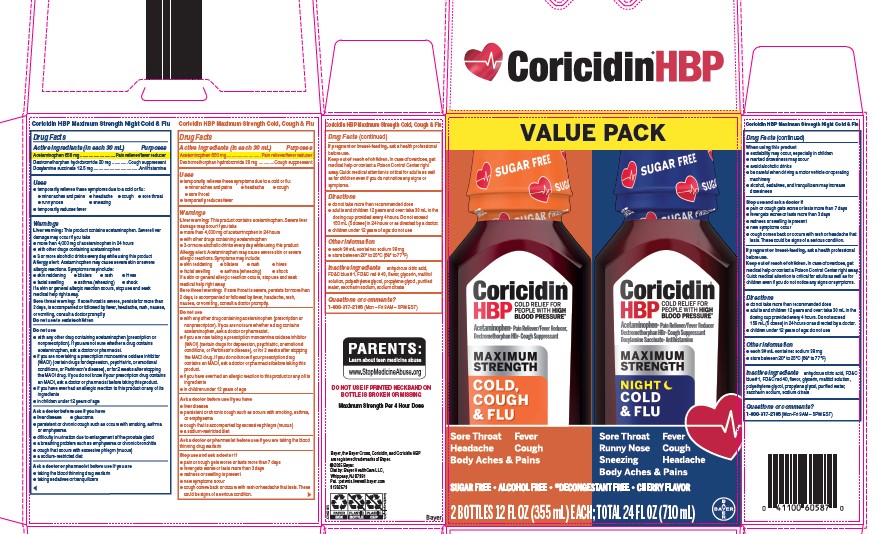 DRUG LABEL: Coricidin HBP Maximum Strength Cold, Cough and Flu
NDC: 11523-0124 | Form: KIT | Route: ORAL
Manufacturer: Bayer HealthCare LLC.
Category: otc | Type: HUMAN OTC DRUG LABEL
Date: 20251204

ACTIVE INGREDIENTS: DEXTROMETHORPHAN HYDROBROMIDE 20 mg/30 mL; ACETAMINOPHEN 650 mg/30 mL; DEXTROMETHORPHAN HYDROBROMIDE 20 mg/30 mL; ACETAMINOPHEN 650 mg/30 mL; DOXYLAMINE SUCCINATE 12.5 mg/30 mL
INACTIVE INGREDIENTS: MALTITOL; POLYETHYLENE GLYCOL, UNSPECIFIED; PROPYLENE GLYCOL; SACCHARIN SODIUM; SODIUM CITRATE; GLYCERIN; FD&C BLUE NO. 1; FD&C RED NO. 40; WATER; ANHYDROUS CITRIC ACID; MALTITOL; POLYETHYLENE GLYCOL, UNSPECIFIED; SACCHARIN SODIUM; SODIUM CITRATE; GLYCERIN; FD&C BLUE NO. 1; FD&C RED NO. 40; WATER; ANHYDROUS CITRIC ACID; PROPYLENE GLYCOL

Coricidin HBP Maximum Strength Cold , Cough & Flu Day/Cold & Flu Night Bundle UIs 1615257/1614785

Product Name

Coricidin HBP Max Strength Cold, Cough, and Flu

Active ingredients (in each 30 mL) | Purposes
Acetaminophen 650 mg | Pain reliever/fever reducer
Dextromethorphan hydrobromide 20 mg | Cough suppressant

Uses

- temporarily relieves these symptoms due to a cold or flu:
  - minor aches and pains
  - headache
  - cough
  - sore throat
- temporarily reduces fever

Warnings
Liver warning: This product contains acetaminophen. Severe liver damage may occur if you take
• more than 4,000 mg of acetaminophen in 24 hours
• with other drugs containing acetaminophen
• 3 or more alcoholic drinks every day while using this product

Allergy alert: Acetaminophen may cause severe skin or severe allergic reactions. Symptoms may include:

- skin reddening
- blisters
- rash
- hives
- facial swelling
- asthma (wheezing)
- shock

If a skin or general allergic reaction occurs, stop use and seek medical help right away.

Sore throat warning: If sore throat is severe, persists for more than 2 days, is accompanied or followed by fever, headache, rash, nausea, or vomiting, consult a doctor promptly.

Do not use

- with any other drug containing acetaminophen (prescription or nonprescription). If you are not sure whether a drug contains acetaminophen,ask a doctor or pharmacist.
- if you are now taking a prescription monoamine oxidase inhibitor (MAOI) (certain drugs for depression, psychiatric, or emotional conditions, or Parkinson's disease), or for 2 weeks after stopping the MAOI drug. If you do not know if your prescription drug contains an MAOI, ask a doctor or pharmacist before taking this product.
- if you have ever had an allergic reaction to this product or any of its ingredients
- in children under 12 years of age

Ask a doctor before use if you have

- liver disease
- persistent or chronic cough such as occurs with smoking, asthma or emphysema
- cough that is accompanied with excessive phlegm (mucus)
- a sodium-restricted diet

Ask a doctor or pharmacist before use if you are taking the blood thinning drug warfarin

Stop use and ask a doctor if

- pain or cough gets worse or lasts more than 7 days
- fever gets worse or lasts more than 3 days
- redness or swelling is present
- new symptoms occur
- cough comes back or occurs with rash or headache that lasts. These could be signs of a serious condition.

PREGNANCY OR BREAST FEEDING

If pregnant or breast-feeding, ask a health professional before use.

Keep out of reach of children. In case of overdose, get medical help or contact a Poison Control Center right away. Quick medical attention is critical for adults as well as for children even if you do not notice any signs or symptoms.

Directions

- do not take more than recommended dose
- adults and children 12 years and over: take 30 mL in the dosing cup provided every 4 hours. Do not exceed 150 mL (5 doses) in 24 hours or as directed by a doctor.
- children under 12 years of age: do not use

Other information
• each 30 mL contains: sodium 38 mg
• store between 20º to 25ºC (68º to 77ºF)

INACTIVE INGREDIENT

Inactive ingredients anhydrous citric acid, FD&C blue #1, FD&C red # 40, flavor, glycerin, maltitol solution, polyethylene glycol, propylene glycol, purified water, saccharin sodium, sodium citrate

Questions or comments? 1-800-317-2165 (Mon – Fri 9AM – 5PM EST)

Product Name

Coricidin HBP Max Strength Night Cold and Flu

Active ingredients (in each 30mL) | Purposes
Acetaminophen 650mg | Pain reliever/fever reducer
Dextromethorphan hydrobromide 20mg | Cough suppressant
Doxylamine succinate 12.5mg | Antihistamine

INDICATIONS AND USAGE

- temporarily relieves these symptoms due to a cold or flu:
- minor aches and pains
- headache
- cough
- sore throat
- runny nose
- sneezing

- temporarily reduces fever

Warnings
Liver warning: This product contains acetaminophen. Severe liver damage may occur if you take
• more than 4,000 mg of acetaminophen in 24 hours
• with other drugs containing acetaminophen
• 3 or more alcoholic drinks every day while using this product

Allergy alert: Acetaminophen may cause severe skin or severe allergic reactions. Symptoms may include:

- skin reddening
- blisters
- rash
- hives
- facial swelling
- asthma (wheezing)
- shock

If a skin or general allergic reaction occurs, stop use and seek medical help right away.

Sore throat warning: If sore throat is severe, persists for more than 2 days, is accompanied or followed by fever, headache, rash, nausea, or vomiting, consult a doctor promptly.

Do not use to sedate children

Do not use

- with any other drug containing acetaminophen (prescription or nonprescription). If you are not sure whether a drug contains acetaminophen,ask a doctor or pharmacist.
- if you are now taking a prescription monoamine oxidase inhibitor (MAOI) (certain drugs for depression, psychiatric, or emotional conditions, or Parkinson's disease), or for 2 weeks after stopping the MAOI drug. If you do not know if your prescription drug contains an MAOI, ask a doctor or pharmacist before taking this product.
- if you have ever had an allergic reaction to this product or any of its ingredients
- in children under 12 years of age

Ask a doctor befpre ise if you have

- liver disease
- glaucoma
- persistent or chronic cough such as occurs with smoking, asthma or emphysema
- difficulty in urination due to enlargement of the prostate gland
- a breathing problem sich as emphysema or chronic bronchitis
- cough that occurs with excessive phlegm (mucus)
- a sodium-restricted diet

Ask a doctor or pharmacist before use if you are

- taking the blood thinning drug warfarin
- taking sedatives or tranquilizers

When using this product

- excitability may occur, especially in children
- marked drowsiness may occur
- avoid alcoholic drinks
- be careful when driving a motor vehicle or operating machinery
- alcohol, sedatives, and tranquilizers may increase drowsiness

Stop use and ask a doctor if

- pain or cough gets worse or lasts more than 7 days
- fever gets worse or lasts more than 3 days
- redness or swelling is present
- new symptoms occur
- cough comes back or occurs with rash or headache that lasts. These could be signs of a serious condition.

PREGNANCY OR BREAST FEEDING

If pregnant or breast-feeding, ask a health professional before use.

Keep out of reach of children. In case of overdose, get medical help or contact a Poison Control Center right away. Quick medical attention is critical for adults as well as for children even if you do not notice any signs or symptoms.

Directions

- do not take more than recommended dose
- adults and children 12 years and over: take 30 mL in the dosing cup provided every 4 hours. Do not exceed 150 mL (5 doses) in 24 hours or as directed by a doctor.
- children under 12 years of age: do not use

Other information
• each 30 mL contains: sodium 38 mg
• store between 20º to 25ºC (68º to 77ºF)

INACTIVE INGREDIENT

Inactive ingredients anhydrous sitric acid, FD&C blue #1, FD&C red#40, flavor, glycerin, maltitol solution, polyethylene glycol, propylene glycol, purified water, saccharin sodium, sodium citrate

Questions or comments? 1-800-317-2165 (Mon – Fri 9AM – 5PM EST)